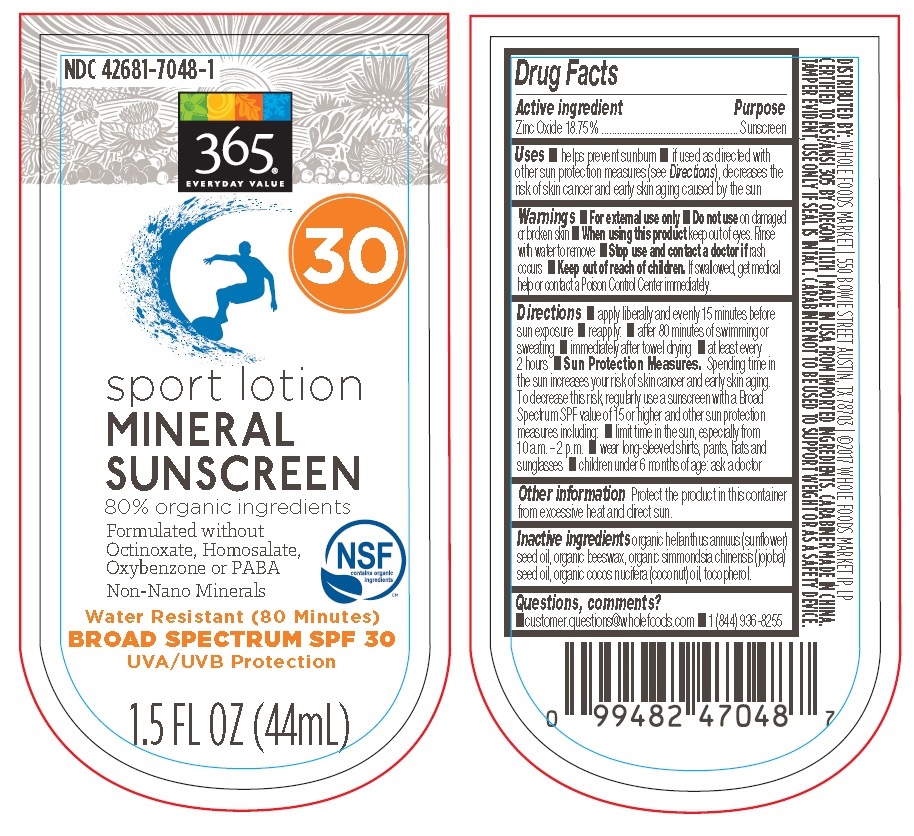 DRUG LABEL: 365 Everyday Value
NDC: 42681-7048 | Form: LOTION
Manufacturer: Whole Foods Market, Inc.
Category: otc | Type: HUMAN OTC DRUG LABEL
Date: 20231103

ACTIVE INGREDIENTS: ZINC OXIDE 8.25 g/44 mL
INACTIVE INGREDIENTS: SUNFLOWER OIL; YELLOW WAX; JOJOBA OIL; COCONUT OIL; TOCOPHEROL

365 EVERYDAY VALUE sport lotion MINERAL SUNSCREEN SPF 30

Drug Facts

Active ingredient
Zinc Oxide 18.75%

Purpose
Sunscreen

INDICATIONS AND USAGE

Uses■ helps prevent sunburn ■ if used as directed with
other sun protection measures (see Directions), decreases the
risk of skin cancer and early skin aging caused by the sun

WARNINGS

Warnings ■ For external use only ■ Do not use on damaged
or broken skin ■ When using this product keep out of eyes. Rinse
with water to remove ■ Stop use and contact a doctor if rash
occurs

■ Keep out of reach of children. If swallowed, get medical
help or contact a Poison Control Center immediately.

DOSAGE AND ADMINISTRATION

Directions ■ apply liberally and evenly 15 minutes before
sun exposure ■ reapply: ■ after 80 minutes of swimming or
sweating ■ immediately after towel drying ■ at least every
2 hours ■ Sun Protection Measures. Spending time in
the sun increases your risk of skin cancer and early skin aging.
To decrease this risk, regularly use a sunscreen with a Broad
Spectrum SPF value of 15 or higher and other sun protection
measures including: ■ limit time in the sun, especially from
10 a.m. – 2 p.m. ■ wear long-sleeved shirts, pants, hats and
sunglasses ■ children under 6 months of age: ask a doctor

Other information Protect the product in this container
from excessive heat and direct sun.

Inactive ingredients organic helianthus annuus (sunflower)
seed oil, organic beeswax, organic simmondsia chinensis (jojoba)
seed oil, organic cocos nucifera (coconut) oil, tocopherol.

Questions, comments?
■ customer.questions@wholefoods.com ■ 1 (844) 936-8255

Principal Display Package

NDC 42681-7048-1

365®
EVERYDAY VALUE

30

sport lotion
MINERAL
SUNSCREEN

80% organic ingredients
Formulated without
Octinoxate, Homosalate,
Oxybenzone or PABA
Non-Nano Minerals

NSF
contains organic
ingredients CF

Water Resistant (80 Minutes)

BROAD SPECTRUM SPF 30
UVA/UVB Protection

1.5 FL OZ (44mL)

DISTRIBUTED BY: WHOLE FOODS MARKET | 550 BOWIE STREET AUSTIN, TX 78703 | ©2017 WHOLE FOODS MARKET IP, LP
CERTIFIED TO NSF/ANSI 305 BY OREGON TILTH | MADE IN USA FROM IMPORTED INGREDIENTS. CARABINER MADE IN CHINA.
TAMPER EVIDENT, USE ONLY IF SEAL IS INTACT. CARABINER NOT TO BE USED TO SUPPORT WEIGHT OR AS A SAFETY DEVICE.

0 99482 47048 7

res